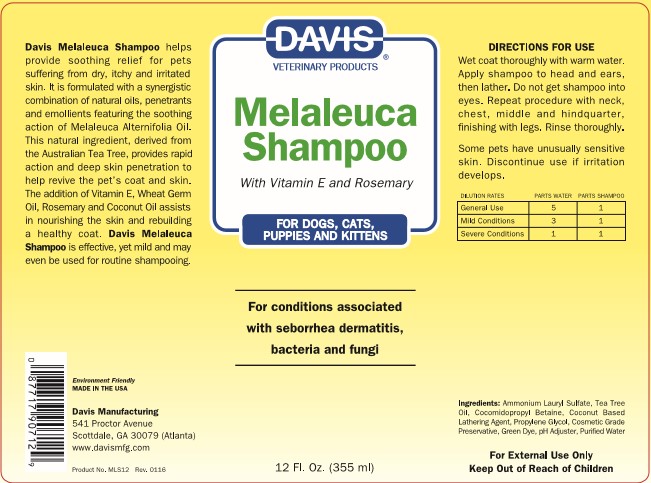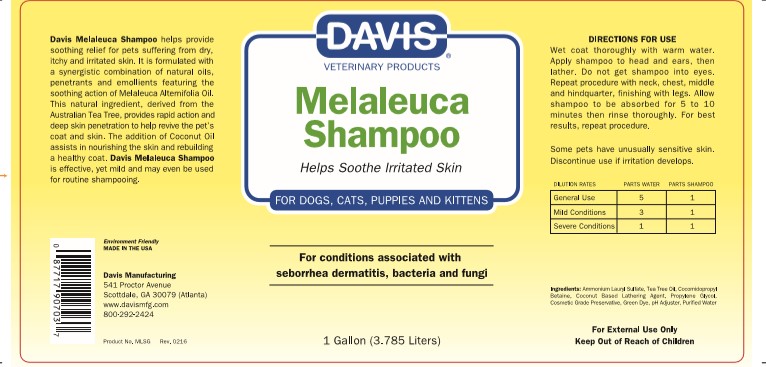 DRUG LABEL: Davis Melaleuca
NDC: 62570-061 | Form: SHAMPOO
Manufacturer: Davis Manufacturing and Packaging Inc
Category: animal | Type: OTC ANIMAL DRUG LABEL
Date: 20191107

ACTIVE INGREDIENTS: TEA TREE OIL 0.7239 g/100 g
INACTIVE INGREDIENTS: AMMONIUM LAURYL SULFATE; COCAMIDOPROPYL BETAINE; COCO MONOETHANOLAMIDE; PROPYLENE GLYCOL; METHYLCHLOROISOTHIAZOLINONE/METHYLISOTHIAZOLINONE MIXTURE; ANHYDROUS CITRIC ACID

Davis Melaleuca Shampoo

DESCRIPTION

Davis Melaleuca Shampoo helps provide soothing relief for pets suffering from dry, itchy and irritated skin. It is formulated with a synergistic combination of natural oils, penetrants and emollients featuring the soothing action of Melaleuca Alternifolia Oil. This natural ingredient, derived from the Australian Tea Tree, provides rapid action and deep skin penetration to help revive the pet's coat and skin. The addition of Vitamin E, Wheat Germ Oil, Rosemary, and Coconut Oil assists in nourishing the skin and rebuilding a healthy coat. Davis Melaleuca Shampoo is effective, yet mild and may even be used for routine shampooing.

Environment Friendly

MADE IN THE USA

Davis Manufacturing

541 Proctor Avenue

Atlanta/Scottdale, GA 30079

www.davismfg.com

DIRECTIONS FOR USE

Wet Coat thoroughly with warm water. Apply shampoo to head and ears, then lather. Do not get shampoo into eyes. Repeat procedure with neck, chest, middle and hindquarter, finish with legs. Rinse thoroughly.

WARNINGS AND PRECAUTIONS

Some pets have unusually sensitive skin. Discontinue use if irritation develops.

DOSAGE FORMS AND STRENGTHS

DILUTION RATES PARTS WATER PARTS SHAMPOO
GENERAL USE | 5 | 1
MILD CONDITIONS | 3 | 1
SEVER CONDITIONS | 1 | 1

INACTIVE INGREDIENT

INGREDIENTS: AMMONIUM LAURYL SULFATE, TEA TREE OIL, COCOMIDOPROPYL BETAINE, COCONUT BASED LATHERING AGENT, PROPYLENE GLYCOL, COSMETIC GRADE PRESERVATIVE, GREEN DYE, pH ADJUSTER, PURIFIED WATER

KEEP OUT OF REACH OF CHILDREN

FOR EXTERNAL USE ONLY

KEEP OUT OF REACH OF CHILDREN

PRINCIPAL DISPLAY FOR 355 ML

DAVIS VETERINARY PRODUCTS

MELALEUCA SHAMPOO

WITH VITAMIN E AND ROSEMARY

FOR DOGS, CATS, PUPPIES AND KITTENS

FOR CONDITIONS ASSOCIATED WITH SEBORREA DERMITIS, BACTERIA AND FUNGI

12 FL. OZ. (355 ML)

PACKAGE LABEL

DAVIS VETERINARY PRODUCTS

MELALEUCA SHAMPOO

WITH VITAMIN E AND ROSEMARY

FOR DOGS, CATS, PUPPIES AND KITTENS

FOR CONDITIONS ASSOCIATED WITH SEBORREA DERMITIS, BACTERIA AND FUNGI

1 GALLON (3.785 LITERS)